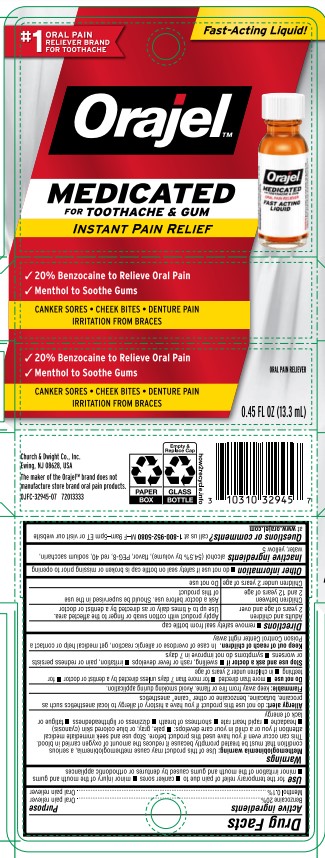 DRUG LABEL: Orajel Medicated for Toothache and Gum, Liquid
NDC: 10237-796 | Form: LIQUID
Manufacturer: Church & Dwight Co., Inc.
Category: otc | Type: HUMAN OTC DRUG LABEL
Date: 20251211

ACTIVE INGREDIENTS: BENZOCAINE 200 mg/1 mL; MENTHOL, UNSPECIFIED FORM 1 mg/1 mL
INACTIVE INGREDIENTS: METHYL SALICYLATE; POLYETHYLENE GLYCOL, UNSPECIFIED; FD&C YELLOW NO. 5; ALCOHOL; SACCHARIN SODIUM; FD&C RED NO. 40; WATER

Orajel Medicated for Toothache and Gum, Liquid

ACTIVE INGREDIENT

Benzocaine 20%

Menthol 0.1%

PURPOSE

Oral Pain Reliever

INDICATIONS AND USAGE

Usefor the temporary relief of pain due to • canker sores • minor injury of the mouth and gums • minor irritation of the mouth and gums caused by dentures or orthodontic appliances

WARNINGS

Methemoglobinemia warning: Use of this product may cuse methemoglobinemia, a serious condition that must be treated promptly becasue it reduces the amount of oxygen carried in the blood. This can occur even if you have used this product before. Stop use and seek immediate medical attention if you or a child in your care develops: • pale, gray or blue colored skin (cyanosis) • headache • rapid heart rate • shortness or breath • dizziness or lightheadedness • fatigue or lack of energy

Allergy Alert:do not use this product if you have a history of allergy to local anesthetics such as procaine, butacaine, benzocaine, or other "caine" anesthetics

Flammable: keep away from fire or flame. Avoid smoking during application.

Do not use• more than directed • for more than 7 days unless directed by a dentist or doctor •for teething •in children under 2 years of age

Stop use and ask a physician if• swelling, rash or fever develops • irritation, pain or redness persists or worsens • symptoms do not improve in 7 days

Keep out of reach of children.

In case of overdose or allergic reaction, get medical help or contact a Poison Control Center right away

DOSAGE AND ADMINISTRATION

Directions •remove imprinted safety seal from bottle cap

Adults and children 2 years of age and over

- Apply product with cotton swab or finger to the affected area. Use up to 4 times daily or as directed by a dentist or doctor

Children under 12 years of age

- Ask a doctor before use. Should be supervised in the use of this product

Children under 2 years of age

- Do not use

Other Information • do not use if safety seal on bottle cap is broken or missing prior to opening

INACTIVE INGREDIENT

Inactive Ingredientsalcohol (54.5% by volume), flavor, PEG-8, red 40, sodium saccarin, water, yellow 5

QUESTIONS

Questions or comment?Call us at 800 952 5080M-F 9am-5pm or visit our website at www orajel.com

PACKAGE LABEL

#1

ORAL PAIN

RELIEVER BRAND

FOR TOOTHACHE

Fast-Acting Liquid!

Orajel

MEDICATED

FORTOOTHACHE & GUM

Instant Pain Relief

•20% Benzocaine to Relieve Oral Pain

•Menthol to Soothe Gums

CANKER SORES • CHEEK BITES • DENTURE PAIN

IRRITATION FROM BRACES

ORAL PAIN RELIEVER

0.45 FL OZ (13.3mL)

ws